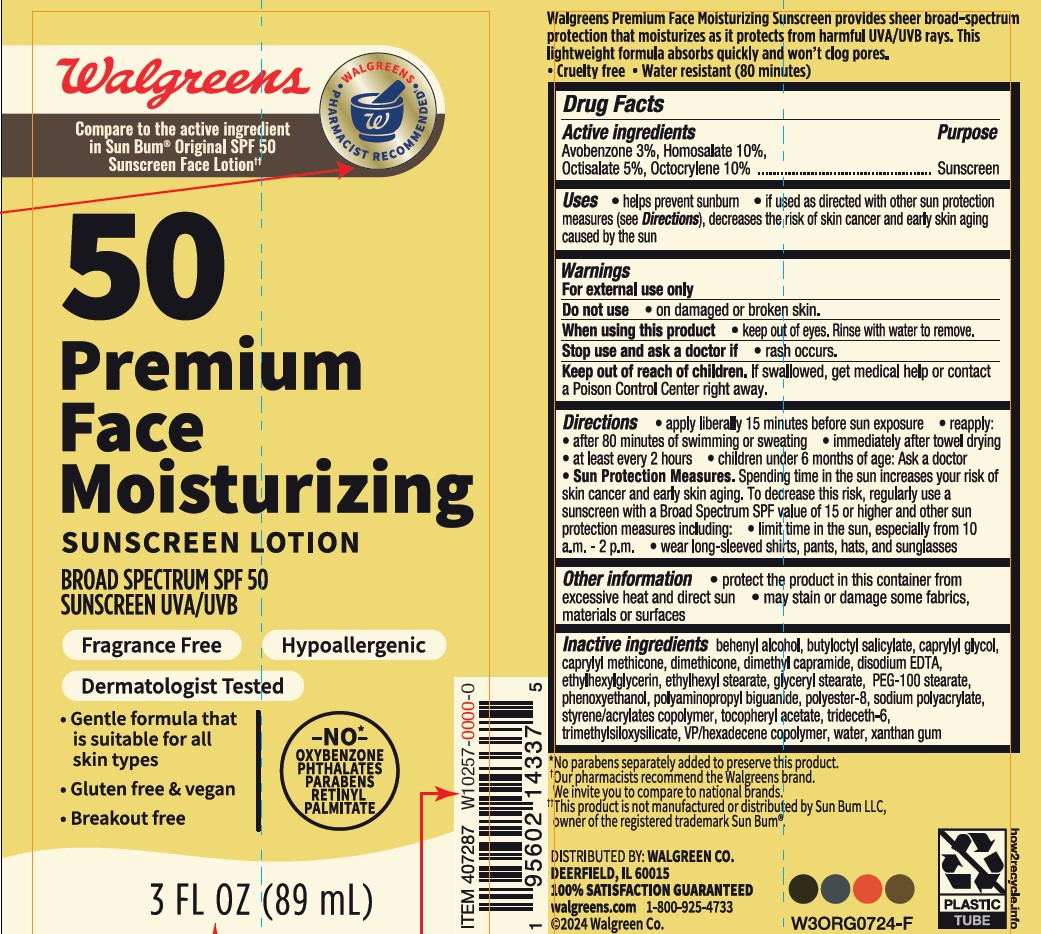 DRUG LABEL: Walgreens 50 Premium Face Moisturizing Sunscreen
NDC: 0363-0388 | Form: LOTION
Manufacturer: WALGREEN COMPANY
Category: otc | Type: HUMAN OTC DRUG LABEL
Date: 20241010

ACTIVE INGREDIENTS: HOMOSALATE 100 mg/1 mL; AVOBENZONE 30 mg/1 mL; OCTOCRYLENE 100 mg/1 mL; OCTISALATE 50 mg/1 mL
INACTIVE INGREDIENTS: CAPRYLYL GLYCOL; DOCOSANOL; CAPRYLYL TRISILOXANE; PEG-100 STEARATE; DIMETHYL CAPRAMIDE; XANTHAN GUM; WATER; EDETATE DISODIUM; PHENOXYETHANOL; ETHYLHEXYL STEARATE; ETHYLHEXYLGLYCERIN; BUTYLOCTYL SALICYLATE; TRIDECETH-6; GLYCERYL 1-STEARATE; SODIUM POLYACRYLATE (8000 MW); .ALPHA.-TOCOPHEROL ACETATE; BUTYL METHACRYLATE/METHYL METHACRYLATE/METHACRYLIC ACID/STYRENE CROSSPOLYMER; DIMETHICONE; POLYAMINOPROPYL BIGUANIDE; POLYESTER-8 (1400 MW, CYANODIPHENYLPROPENOYL CAPPED); HEXADECYL POVIDONE

Walgreens 50 Premium Face Moisturizing Sunscreen Lotion

Active ingredients

Avobenzone 3.0%,

Homosalate 10.0%,

Octisalate 5.0%

Octocrylene 10.0%

Purpose

Sunscreen

Uses

- helps prevent sunburn
- if used as directed with other sun protection measures (see Directions), decreases the risk of skin cancer and early skin aging caused by the sun

Warnings

For external use only

Do not use

• on damaged or broken skin.

When using this product

• keep out of eyes. Rinse with water to remove.

Stop use and ask a doctor if

• rash occurs.

Keep out of reach of children.

If swallowed, get medical help or contact a Poison Control Center right away.

Directions

- apply liberally 15 minutes before sun exposure
- use a water resistant sunscreen if swimming or sweating
- reapply at least every 2 hours
- children under 6 months of age: Ask a doctor
- Sun Protection Measures. Spending time in the sun increases your risk of skin cancer and early skin aging. To decrease this risk, regularly use a sunscreen with a Broad Spectrum SPF value of 15 or higher and other sun protection measures including:

• limit time in the sun, especially from 10 a.m. - 2 p.m.

• wear long-sleeved shirts, pants, hats, and sunglasses

Other information

- protect the product in this container from excessive heat and direct sun
- may stain or damage some fabrics, materials or surfaces

Inactive ingredients

behenyl alcohol, butyloctyl salicylate, caprylyl glycol, caprylyl methicone, dimethicone, dimethyl capramide, disodium EDTA, ethylhexylglycerin, ethylhexyl stearate, glyceryl stearate, PEG-100 stearate, phenoxyethanol, polyaminopropyl biguanide, polyester-8, sodium polyacrylate, styrene/acrylates copolymer, tocopheryl acetate, trideceth-6, trimethylsiloxysilicate, VP/hexadecene copolymer, water, xanthan gum